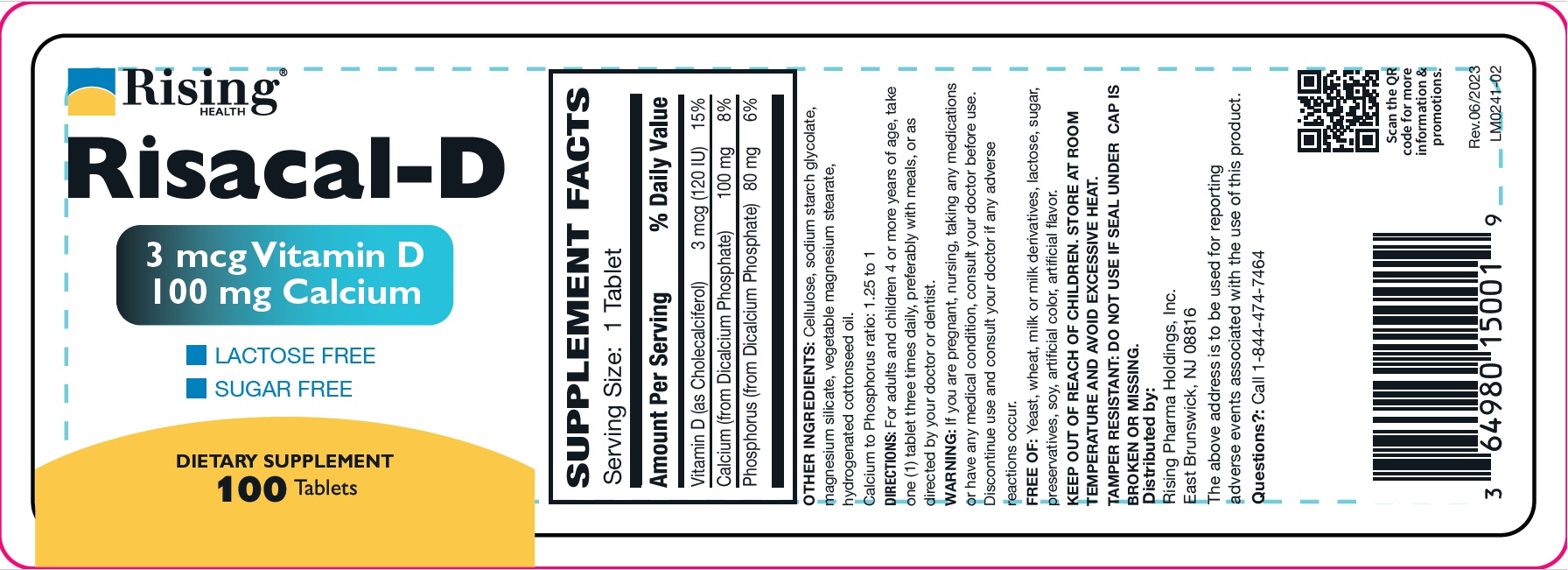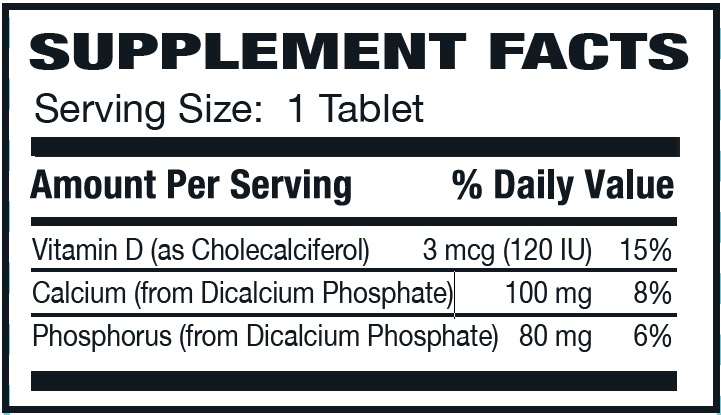 DRUG LABEL: Risacal-D
NDC: 64980-150 | Form: TABLET
Manufacturer: Rising Pharma Holdings, Inc.
Category: other | Type: DIETARY SUPPLEMENT
Date: 20250616

ACTIVE INGREDIENTS: CHOLECALCIFEROL 3 ug/1 1; CALCIUM 100 mg/1 1; PHOSPHORUS 80 mg/1 1
INACTIVE INGREDIENTS: POWDERED CELLULOSE; SODIUM STARCH GLYCOLATE TYPE A; MAGNESIUM SILICATE; MAGNESIUM STEARATE; HYDROGENATED COTTONSEED OIL

Risacal-D, Dietary Supplement, 100 Tablets

HEALTH CLAIM

Other ingredients: Cellulose, sodium starch glycolate, magnesium silicate, vegetable magnesium stearate, hydrogenated cottonseed oil.

Calcium to Phosphorus ratio: 1.25 to 1

DOSAGE AND ADMINISTRATION

DIRECTIONS: For adults and children 4 or more years of age, take one (1) tablet three times daily, preferably with meals, or as directed by your doctor or dentist.

WARNINGS

WARNING: If you are pregnant, nursing, taking any medications or have any medical condition, consult your doctor before use.
Discontinue use and consult your doctor if any adverse reactions occur.

FREE OF: Yeast, wheat, milk or milk derivatives, lactose, sugar, preservatives, soy, artificial color, artificial flavor.

SAFE HANDLING WARNING

KEEP OUT OF THE REACH OF CHILDREN.

STORE AT ROOM TEMPERATURE AND AVOID EXCESSIVE HEAT.

TAMPER RESISTANT: DO NOT USE IF SEAL UNDER CAP IS BROKEN OR MISSING.

Distributed by:

Rising Pharma Holdings, Inc.
East Brunswick, NJ 08816

The above address is to be used for reporting adverse events associated with the use of this product.

Questions?:Call 1-844-474-7464

Rev. 06/2023

PACKAGE LABEL.PRINCIPAL DISPLAY PANEL

Risacal-D Tablets

DIETARY SUPPLEMENT

100 Tablets

Bottle Label (64980-150-01)